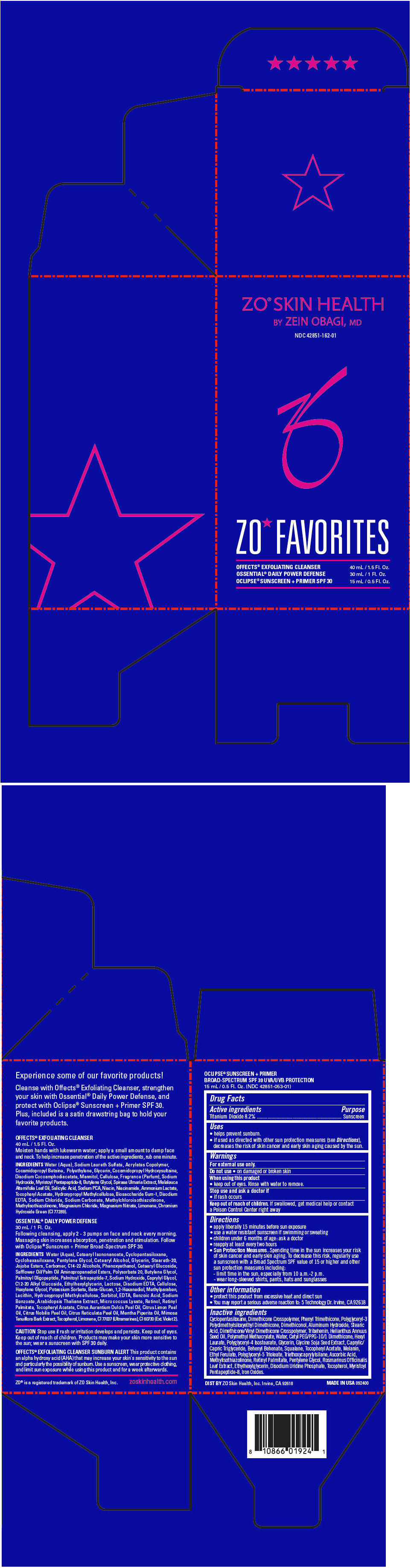 DRUG LABEL: ZO Skin Health ZO Favorites (Mothers Day GWP)
NDC: 42851-162 | Form: KIT | Route: TOPICAL
Manufacturer: ZO Skin Health, Inc.
Category: otc | Type: HUMAN OTC DRUG LABEL
Date: 20200616

ACTIVE INGREDIENTS: TITANIUM DIOXIDE 82 mg/1 mL
INACTIVE INGREDIENTS: CYCLOMETHICONE 5; DIMETHICONE CROSSPOLYMER (450000 MPA.S AT 12% IN CYCLOPENTASILOXANE); PHENYL TRIMETHICONE; POLYGLYCERYL-3 POLYDIMETHYLSILOXYETHYL DIMETHICONE (4000 MPA.S); ALUMINUM HYDROXIDE; STEARIC ACID; DIMETHICONE/VINYL DIMETHICONE CROSSPOLYMER (SOFT PARTICLE); TRIBEHENIN; SUNFLOWER OIL; POLY(METHYL METHACRYLATE; 450000 MW); WATER; HEXYL LAURATE; POLYGLYCERYL-4 ISOSTEARATE; GLYCERIN; MEDIUM-CHAIN TRIGLYCERIDES; BEHENYL BEHENATE; SQUALANE; .ALPHA.-TOCOPHEROL ACETATE; MELANIN SYNTHETIC (TYROSINE, PEROXIDE); ETHYL FERULATE; TRIETHOXYCAPRYLYLSILANE; ASCORBIC ACID; METHYLISOTHIAZOLINONE; VITAMIN A PALMITATE; PENTYLENE GLYCOL; ROSEMARY; ETHYLHEXYLGLYCERIN; URIDINE MONOPHOSPHATE DISODIUM; TOCOPHEROL; FERRIC OXIDE RED

ZO® Skin Health ZO® Favorites (Mother's Day GWP)
NDC 42851-162

Drug Facts

Active ingredients

Titanium Dioxide 8.2%

Purpose

Sunscreen

Uses

- helps prevent sunburn.
- if used as directed with other sun protection measures (see Directions), decreases the risk of skin cancer and early skin aging caused by the sun.

Warnings

For external use only.

Do not use

- on damaged or broken skin

When using this product

- keep out of eyes. Rinse with water to remove.

Stop use and ask a doctor if

- if rash occurs

Keep out of reach of children. If swallowed, get medical help or contact a Poison Control Center right away

Directions

- apply liberally 15 minutes before sun exposure
- use a water resistant sunscreen if swimming or sweating
- children under 6 months of age: ask a doctor
- reapply at least every two hours
- Sun Protection Measures. Spending time in the sun increases your risk of skin cancer and early skin aging. To decrease this risk, regularly use a sunscreen with a Broad Spectrum SPF value of 15 or higher and other sun protection measures including:
  - limit time in the sun, especially from 10 a.m.-2 p.m.
  - wear long-sleeved shirts, pants, hats and sunglasses

Other information

- protect this product from excessive heat and direct sun
- You may report a serious adverse reaction to: 5 Technology Dr. Irvine, CA 92618

Inactive ingredients

Cyclopentasiloxane, Dimethicone Crosspolymer, Phenyl Trimethicone, Polyglyceryl-3 Polydimethylsiloxyethyl Dimethicone, Dimethiconol, Aluminum Hydroxide, Stearic Acid, Dimethicone/Vinyl Dimethicone Crosspolymer, Tribehenin, Helianthus Annuus Seed Oil, Polymethyl Methacrylate, Water, Cetyl PEG/PPG-10/1 Dimethicone, Hexyl Laurate, Polyglyceryl-4 Isostearate, Glycerin, Glycine Soja Seed Extract, Caprylic/Capric Triglyceride, Behenyl Behenate, Squalane, Tocopheryl Acetate, Melanin, Ethyl Ferulate, Polyglyceryl-5 Trioleate, Triethoxycaprylylsilane, Ascorbic Acid, Methylisothiazolinone, Retinyl Palmitate, Pentylene Glycol, Rosmarinus Officinalis Leaf Extract, Ethylhexylglycerin, Disodium Uridine Phosphate, Tocopherol, Myristoyl Pentapeptide-8, Iron Oxides.

DIST BY ZO Skin Health, Inc. Irvine, CA 92618

PRINCIPAL DISPLAY PANEL - Kit Carton

ZO® SKIN HEALTH
BY ZEIN OBAGI, MD

NDC 42851-162-01

ZO★ FAVORITES

OFFECTS® EXFOLIATING CLEANSER
40 mL / 1.5 Fl. Oz.
OSSENTIAL® DAILY POWER DEFENSE
30 mL / 1 Fl. Oz.
OCLIPSE® SUNSCREEN + PRIMER SPF 30
15 mL / 0.5 Fl. Oz.